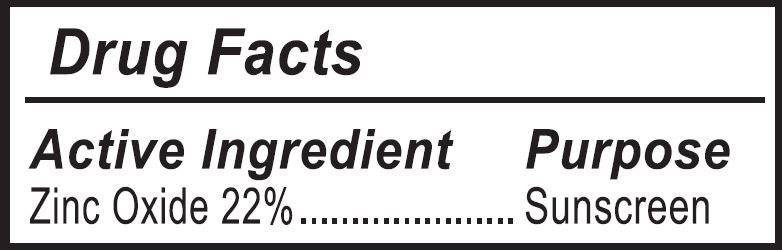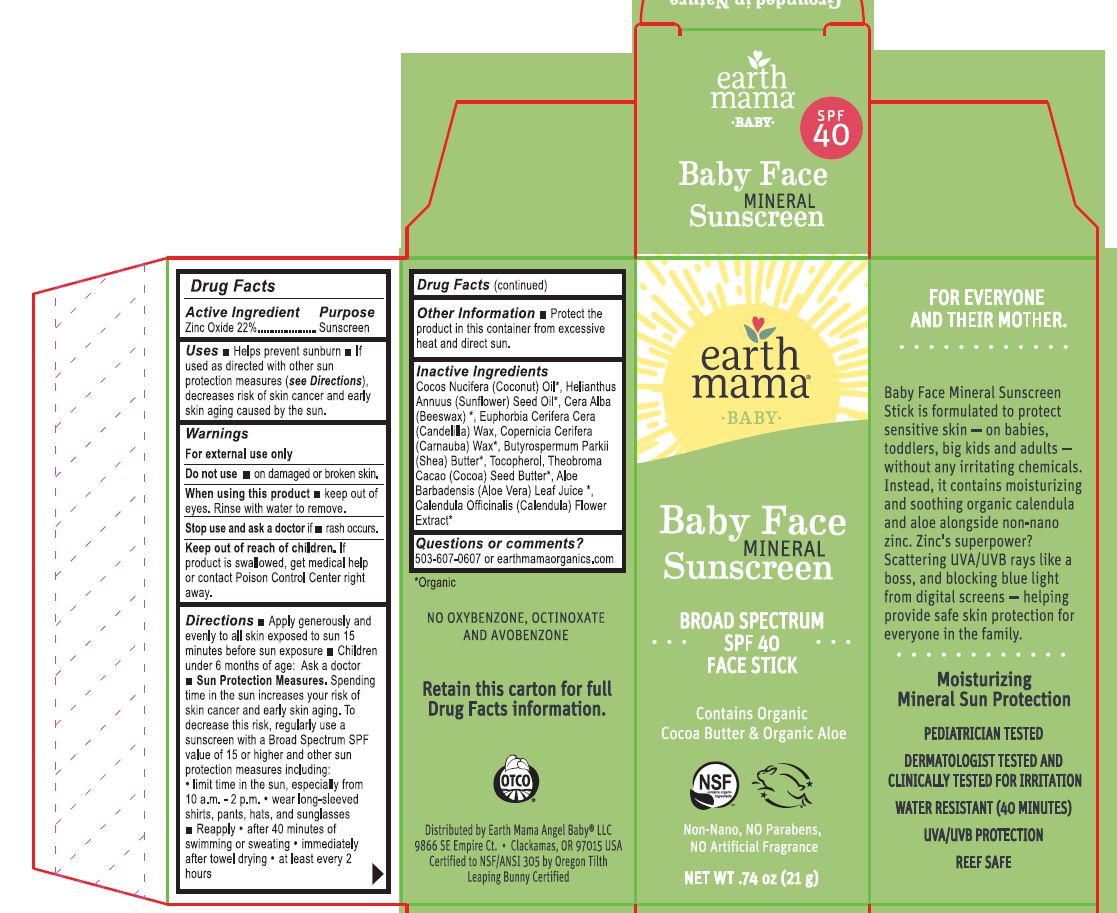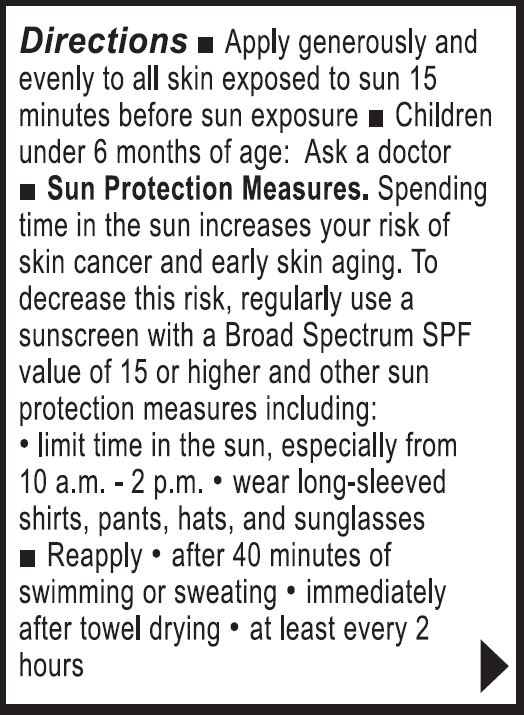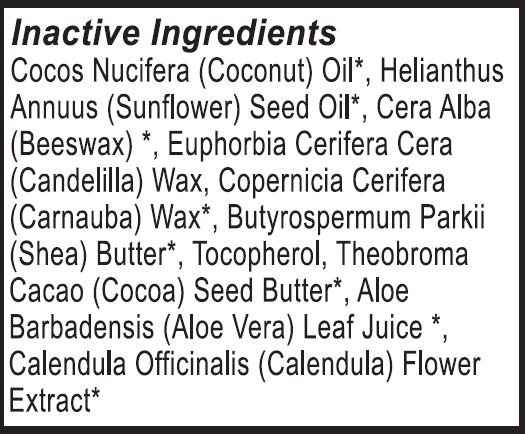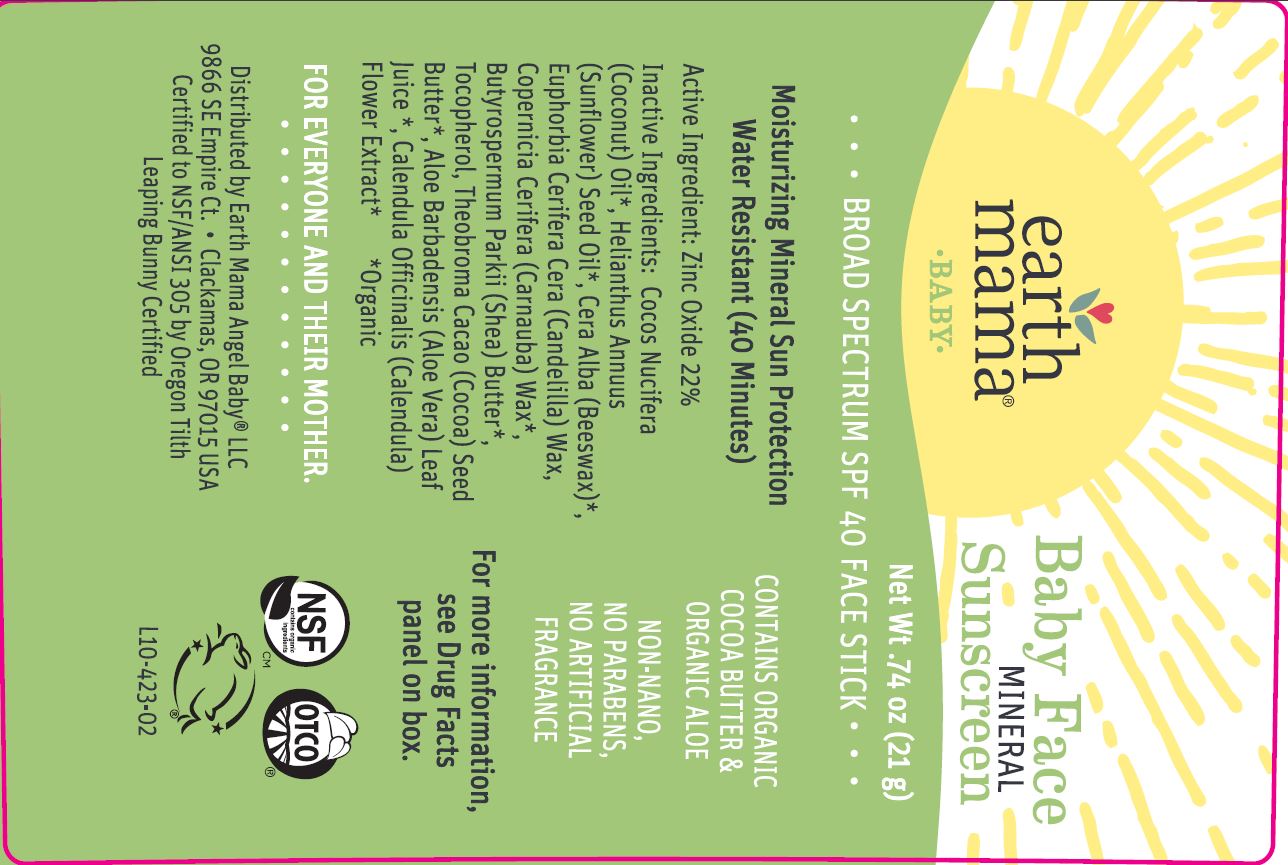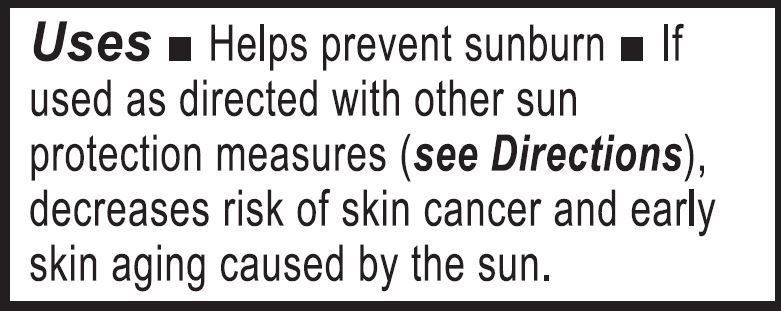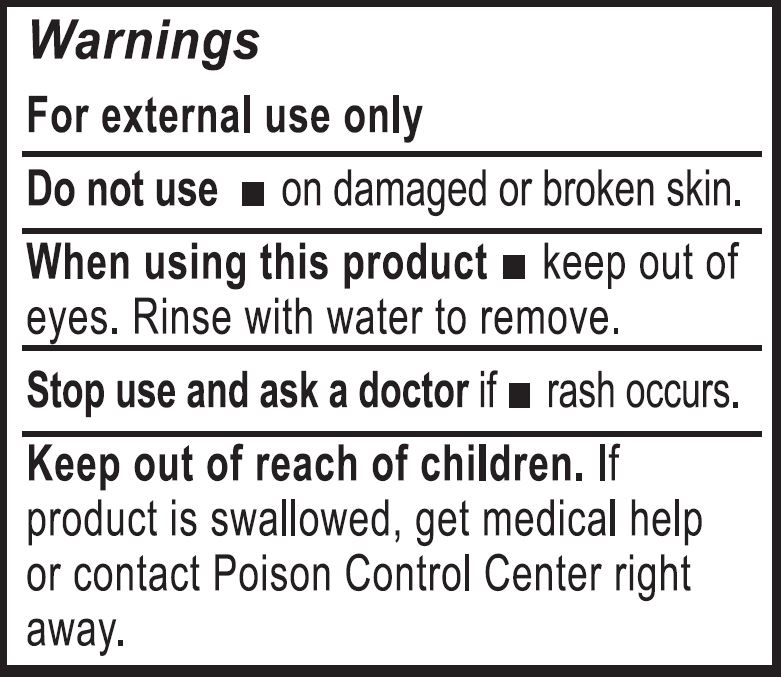 DRUG LABEL: Baby Face Stick Mineral Sunscreen SPF 40
NDC: 62932-261 | Form: STICK
Manufacturer: Private Label Select Ltd CO
Category: otc | Type: HUMAN OTC DRUG LABEL
Date: 20211231

ACTIVE INGREDIENTS: ZINC OXIDE 22 g/100 g
INACTIVE INGREDIENTS: WHITE WAX; CANDELILLA WAX; CARNAUBA WAX; SUNFLOWER OIL; ALOE VERA LEAF; CALENDULA OFFICINALIS FLOWER; SHEA BUTTER; COCOA BUTTER; COCONUT OIL; .BETA.-TOCOPHEROL; .GAMMA.-TOCOPHEROL; .ALPHA.-TOCOPHEROL, D-; .DELTA.-TOCOPHEROL

Earth Mama, Baby Face (Stick) Mineral Sunscreen, SPF 40